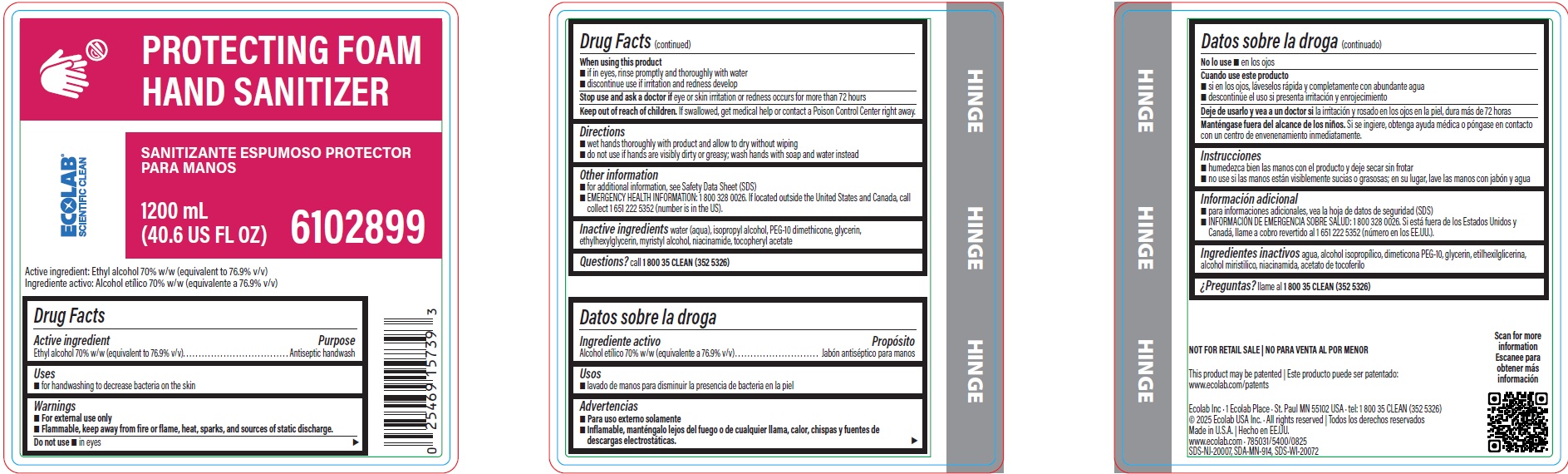 DRUG LABEL: ESC Protecting Foam Hand Sanitizer
NDC: 47593-667 | Form: SOLUTION
Manufacturer: Ecolab Inc.
Category: otc | Type: HUMAN OTC DRUG LABEL
Date: 20260129

ACTIVE INGREDIENTS: ALCOHOL 76.9 mL/100 mL
INACTIVE INGREDIENTS: WATER; ISOPROPYL ALCOHOL; BIS-PEG-12 DIMETHICONE (500 MPA.S); GLYCERIN; ETHYLHEXYLGLYCERIN; MYRISTYL ALCOHOL; NIACINAMIDE; .ALPHA.-TOCOPHEROL ACETATE

Drug Facts

Active Ingredient

Ethyl alcohol 70% w/w (equivalent to 76.9% v/v)

Purpose

Antiseptic handwash

Uses

- for handwashing to decrease bacteria on the skin

Warnings

- For external use only
- FLAMMABLE, keep away from fire or flame, heat, sparks and sources of static discharge

Do not use

- in eyes

When using this product

- if in eyes, rinse promptly and thoroughly with water
- discontinue use if irritation and redness develop

Stop use and ask a doctor if eye or skin irritation or redness occurs for more than 72 hours.

Keep out of reach of children. If swallowed, get medical help or contact a Poison Control Center right away.

Directions

- wet hands thoroughly with product and allow to dry without wiping
- do not use if hands are visibly dirty or greasy; wash hands with soap and water instead.

Other information

- for additional information, see Safety Data Sheet (SDS)
- EMERGENCY HEALTH INFORMATION: 1 800 328 0026. If located outside the United States and Canada, call collect 1 651 222 5352 (number is in the US).

INACTIVE INGREDIENT

Inactive ingredients water (aqua), isopropyl alcohol, PEG-10 dimethicone, glycerin, ethylhexylglycerin, myristyl alcohol, niacinamide, tocopheryl acetate

Questions?

call 1-800-35-CLEAN (352-5326)

Representative label and principal display panel

ECOLAB SCIENTIFIC CLEAN

PROTECTING FOAM

HAND SANITIZER

1200 mL

(40.6 US FL OZ) 6102899

Active ingredient: Ethyl alcohol 70% w/w (equivalent to 76.9% v/v)

Ecolab Inc · 1 Ecolab Place · St. Paul MN 55102 USA · tel: 1 800 35 CLEAN (352 5326)

© 2025 Ecolab USA Inc. · All rights reserved

Made in U.S.A.

www.ecolab.com · 785031/5400/0825

SDS-NJ-20007, SDA-MN-914, SDS-WI-20072